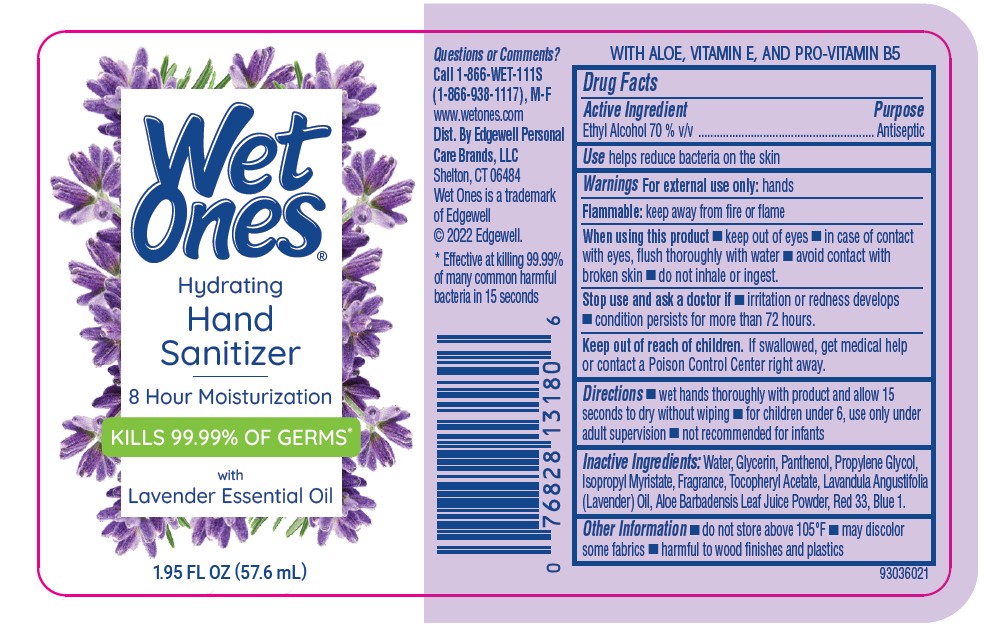 DRUG LABEL: Wet Ones Hand Sanitizer Mist Lavender Blossom
NDC: 63354-270 | Form: AEROSOL, SPRAY
Manufacturer: Edgewell Personal Care Brands LLC
Category: otc | Type: HUMAN OTC DRUG LABEL
Date: 20250917

ACTIVE INGREDIENTS: ALCOHOL 63.2 mL/100 mL
INACTIVE INGREDIENTS: WATER; GLYCERIN; PANTHENOL; ISOPROPYL MYRISTATE; .ALPHA.-TOCOPHEROL ACETATE; LAVENDER OIL; FD&C BLUE NO. 1; PROPYLENE GLYCOL; D&C RED NO. 33; ALOE VERA LEAF

Active Ingredient

Ethyl Alcohol 70 % v/v

Purpose

Antiseptic

Use

helps reduce bacteria on the skin

Warnings

For external use only: hands

Flammable: keep away from fire or flame

When using this product

• keep out of eyes • in case of contact with eyes, flush thoroughly with water • avoid contact with broken skin • do not inhale or ingest.

Stop use and ask a doctor if

• irritation or redness develops • condition persists for more than 72 hours.

Keep out of reach of children.

If swallowed, get medical help or contact a Poison Control Center right away.

Directions

• wet hands thoroughly with product and allow 15 seconds to dry without wiping • for children under 6, use only under adult supervision • not recommended for infants

Inactive Ingredients:

Water, Glycerin, Panthenol, Propylene Glycol, Isopropyl Myristate, Fragrance, Tocopheryl Acetate, Lavandula Angustifolia (Lavender) Oil, Aloe Barbadensis Leaf Juice Powder, Red 33, Blue 1.

Other Informations

• do not store above 105°F • may discolor some fabrics • harmful to wood finishes and plastics

Principal Display Panel

Wet
Ones
Hydrating
Hand
Sanitizer
8 Hour Moisturization
KILLS 99.99% OF GERMS
With
Lavender Essential Oil
1.95 FL OZ (57.6 mL)